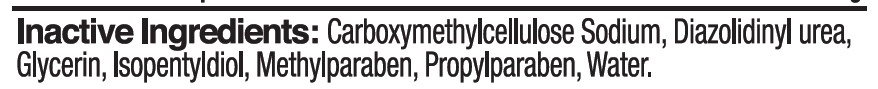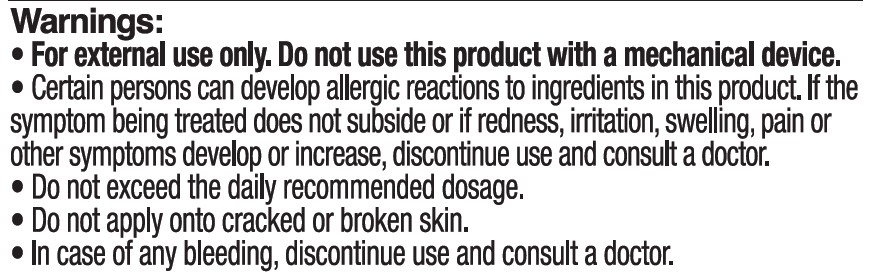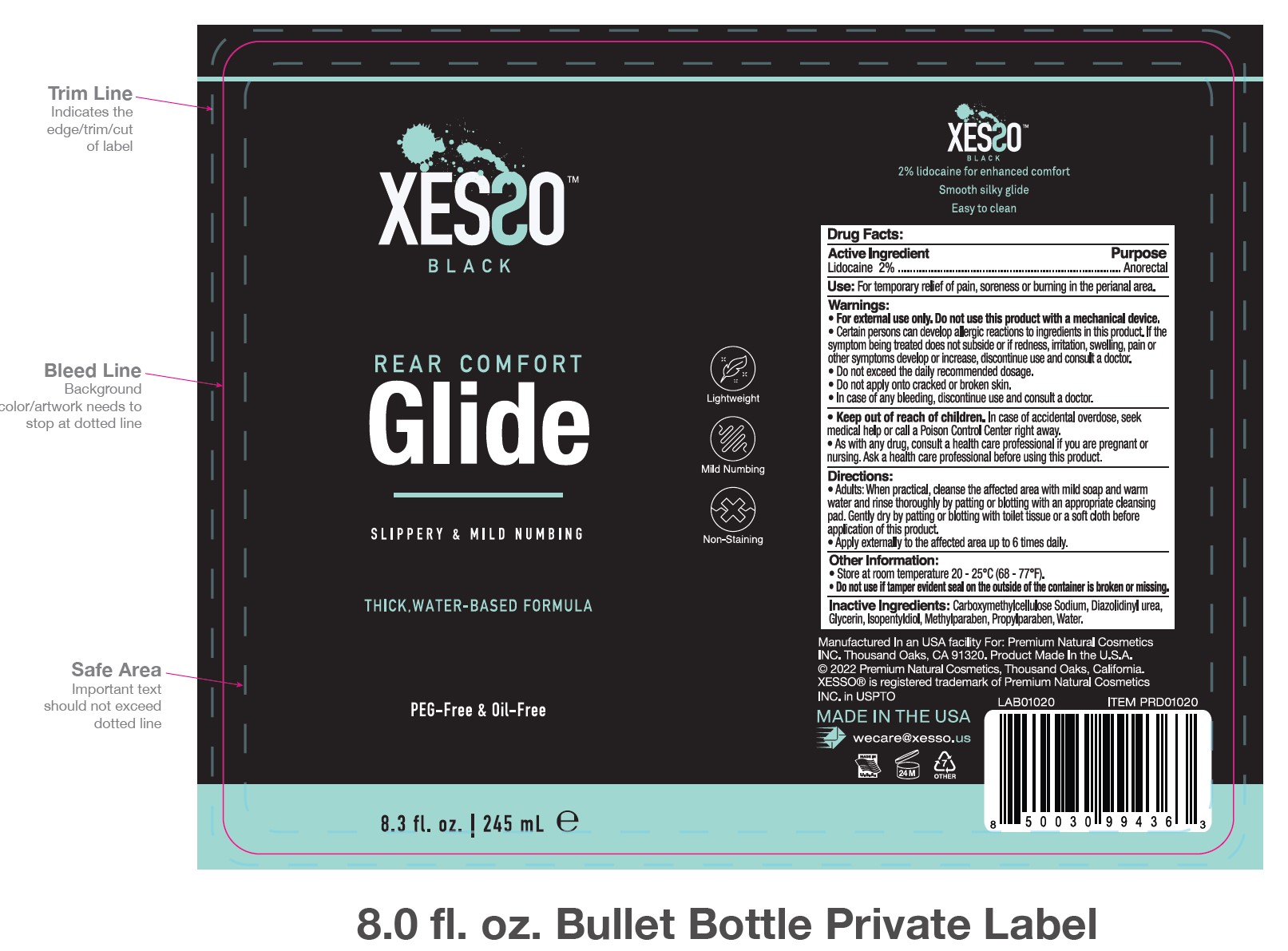 DRUG LABEL: Xesso Rear Comfort Glide
NDC: 81777-104 | Form: GEL
Manufacturer: PREMIUM NATURAL COSMETICS INC
Category: otc | Type: HUMAN OTC DRUG LABEL
Date: 20251022

ACTIVE INGREDIENTS: LIDOCAINE HYDROCHLORIDE 2.35 g/100 mL
INACTIVE INGREDIENTS: ISOPENTYLDIOL; DIAZOLIDINYL UREA; GLYCERIN; METHYLPARABEN; PROPYLPARABEN; WATER; CARBOXYMETHYLCELLULOSE SODIUM

Xesso Rear Comfort Glide 2% Lidocaine

Active Ingredient

Lidocaine 2%

Ask a doctor

As with any drug, consult a health care professional if you are pregnant or nursing. Ask a health care professional before using this product.

Purpose

Anorectal

Use

For temporary relief of pain, soreness, or burning in the perianal area.

Keep out of reach of children. If case of accidental overdose, seek medical help or call a Poison Control Center right away.

Sop Use

Certain persons can develop allergic reactions to ingredients in this product. If the symptom being treated does not subside of if redness, swelling, pain, or other symptoms develop or increase, discontinue use and consult a doctor.

Directions

- Adults: When practical, cleanse the affected area with mild soap and warm water and rinse thoroughly by patting or blotting with an appropriate cleansing pad. Gently dry by patting or blotting with toilet tissue or a soft cloth before application of this product.
- Apply externally to the affected are up to 6 times daily.

Other Information

Store at room temperature 20 - 25 C (68 F - 77F)